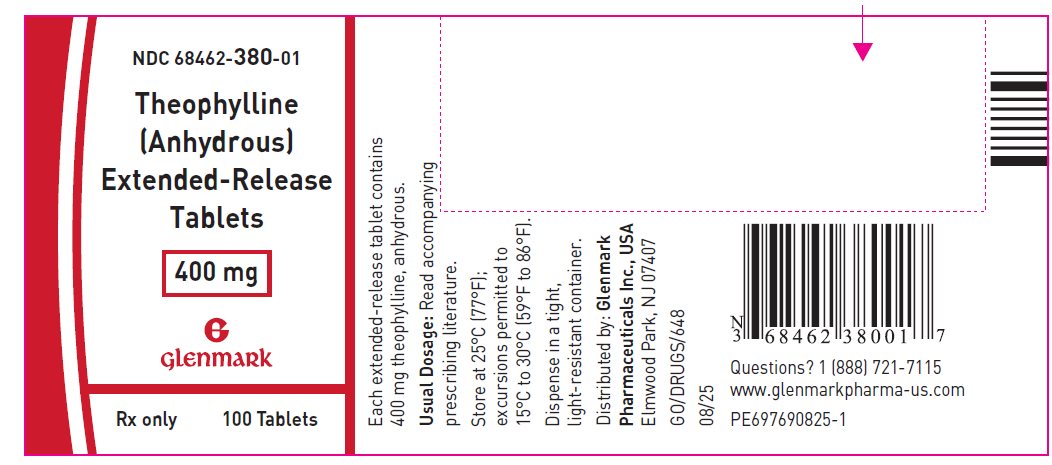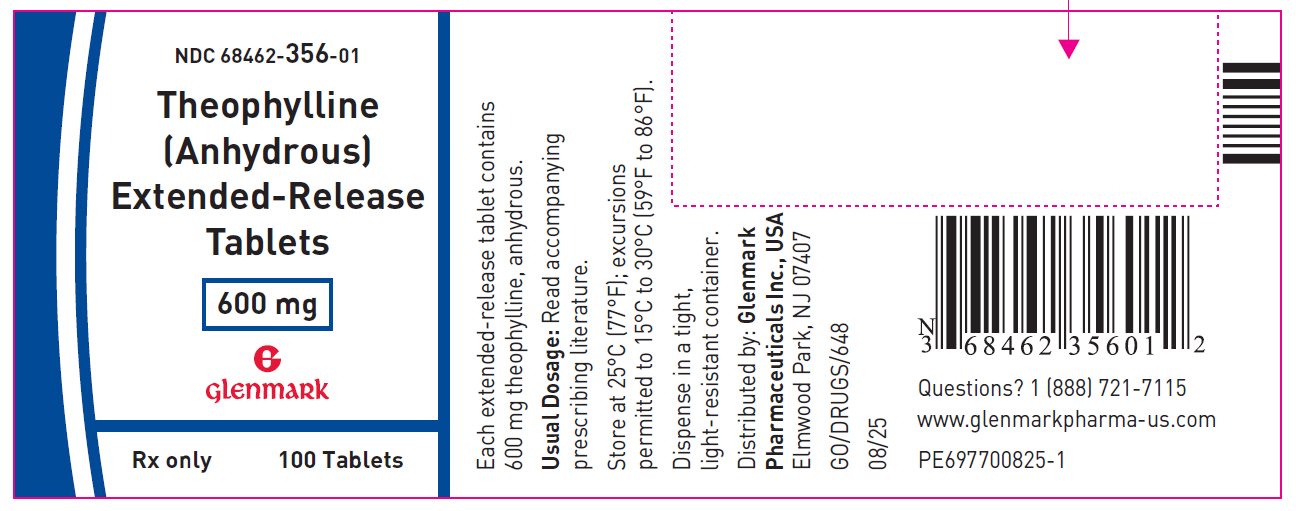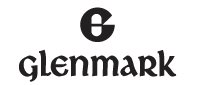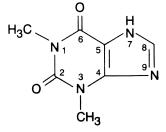 DRUG LABEL: Theophylline
NDC: 68462-380 | Form: TABLET, EXTENDED RELEASE
Manufacturer: Glenmark Pharmaceuticals Inc., USA
Category: prescription | Type: HUMAN PRESCRIPTION DRUG LABEL
Date: 20260129

ACTIVE INGREDIENTS: THEOPHYLLINE ANHYDROUS 400 mg/1 1
INACTIVE INGREDIENTS: CETOSTEARYL ALCOHOL; HYDROXYETHYL CELLULOSE (4000 MPA.S AT 1%); MAGNESIUM STEARATE; POVIDONE, UNSPECIFIED; TALC

Theophylline (Anhydrous) Extended Release Tablets 400 mg and 600 mg

DESCRIPTION

Theophylline (anhydrous) Extended-Release Tablets in a controlled-release system allows a 24-hour dosing interval for appropriate patients.

Theophylline is structurally classified as a methylxanthine. It occurs as a white, odorless, crystalline powder with a bitter taste. Anhydrous theophylline has the chemical name 1H-purine-2,6-dione, 3,7-dihydro-1,3-dimethyl-, and is represented by the following structural formula:

The molecular formula of anhydrous theophylline is C7H8N4O2 with a molecular weight of 180.17 g/mol.

Each extended-release tablet for oral administration contains 400 or 600 mg of anhydrous theophylline.

Inactive Ingredients: cetostearyl alcohol, hydroxyethyl cellulose, magnesium stearate, povidone and talc.

CLINICAL PHARMACOLOGY

Mechanism of Action

Theophylline has two distinct actions in the airways of patients with reversible obstruction; smooth muscle relaxation (i.e., bronchodilation) and suppression of the response of the airways to stimuli (i.e., non-bronchodilator prophylactic effects). While the mechanisms of action of theophylline are not known with certainty, studies in animals suggest that bronchodilatation is mediated by the inhibition of two isozymes of phosphodiesterase (PDE III and, to a lesser extent, PDE IV) while non-bronchodilator prophylactic actions are probably mediated through one or more different molecular mechanisms, that do not involve inhibition of PDE III or antagonism of adenosine receptors. Some of the adverse effects associated with theophylline appear to be mediated by inhibition of PDE III (e.g., hypotension, tachycardia, headache, and emesis) and adenosine receptor antagonism (e.g., alterations in cerebral blood flow).

Theophylline increases the force of contraction of diaphragmatic muscles. This action appears to be due to enhancement of calcium uptake through an adenosine-mediated channel.

Serum Concentration-Effect Relationship

Bronchodilation occurs over the serum theophylline concentration range of 5 to 20 mcg/mL. Clinically important improvement in symptom control has been found in most studies to require peak serum theophylline concentrations >10 mcg/mL, but patients with mild disease may benefit from lower concentrations. At serum theophylline concentrations >20 mcg/mL, both the frequency and severity of adverse reactions increase. In general, maintaining peak serum theophylline concentrations between 10 and 15 mcg/mL will achieve most of the drug’s potential therapeutic benefit while minimizing the risk of serious adverse events.

Pharmacokinetics

Overview:

Theophylline is rapidly and completely absorbed after oral administration in solution or immediate-release solid oral dosage form. Theophylline does not undergo any appreciable pre-systemic elimination, distributes freely into fat-free tissues, and is extensively metabolized in the liver.

The pharmacokinetics of theophylline vary widely among similar patients and cannot be predicted by age, sex, body weight or other demographic characteristics. In addition, certain concurrent illnesses and alterations in normal physiology (see Table I) and co-administration of other drugs (see Table II) can significantly alter the pharmacokinetic characteristics of theophylline. Within-subject variability in metabolism has also been reported in some studies, especially in acutely ill patients. It is, therefore, recommended that serum theophylline concentrations be measured frequently in acutely ill patients (e.g., at 24-hr intervals) and periodically in patients receiving long-term therapy, e.g., at 6 to 12 month intervals. More frequent measurements should be made in the presence of any condition that may significantly alter theophylline clearance (see PRECAUTIONS, Laboratory Tests).

TABLE I. Mean and range of total body clearance and half-life of theophylline related to age and altered physiological states [For various North American patient populations from literature reports. Different rates of elimination and consequent dosage requirements have been observed among other peoples.] .
Population Characteristics | Total body clearance [Clearance represents the volume of blood completely cleared of theophylline by the liver in one minute. Values listed were generally determined at serum theophylline concentrations <20 mcg/mL; clearance may decrease and half-life may increase at higher serum concentrations due to non-linear pharmacokinetics.] mean (range) [Reported range or estimated range (mean ±2 SD) where actual range not reported.] (mL/kg/min) | Half-life mean (range) (hr)
Age
Premature neonates
postnatal age 3 to 15 days | 0.29 (0.09 to 0.49) | 30 (17 to 43)
postnatal age 25 to 57 days | 0.64 (0.04 to 1.2) | 20 (9.4 to 30.6)
Term infants
postnatal age 1 to 2 days | NR [NR = not reported or not reported in a comparable format.] | 25.7 (25 to 26.5)
postnatal age 3-30 weeks | NR | 11 (6 to 29)
Children
1 to 4 years | 1.7 (0.5 to 2.9) | 3.4 (1.2 to 5.6)
4 to 12 years | 1.6 (0.8 to 2.4) | NR
13 to 15 years | 0.9 (0.48 to 1.3) | NR
6 to 17 years | 1.4 (0.2 to 2.6) | 3.7 (1.5 to 5.9)
Adults (16 to 60 years)
otherwise healthy non-smoking asthmatics | 0.65 (0.27 to 1.03) | 8.7 (6.1 to 12.8)
Elderly (>60 years)
non-smokers with normal cardiac, liver, and renal function | 0.41 (0.21 to 0.61) | 9.8 (1.6 to 18)
Concurrent illness or altered physiological state
Acute pulmonary edema | 0.33 [Median] (0.07 to 2.45) | 19 (3.1 to 82)
COPD->60 years, stable non-smoker > 1 year | 0.54 (0.44 to 0.64) | 11 (9.4 to 12.6)
COPD with cor pulmonale | 0.48 (0.08 to 0.88) | NR
Cystic fibrosis (14 to 28 years) | 1.25 (0.31 to 2.2) | 6.0 (1.8 to 10.2)
Fever associated with acute viral respiratory illness (children 9 to 15 years) | NR | 7.0 (1.0 to 13)
Liver disease
cirrhosis | 0.31 (0.1 to 0.7) | 32 (10 to 56)
acute hepatitis | 0.35 (0.25 to 0.45) | 19.2 (16.6 to 21.8)
cholestasis | 0.65 (0.25 to 1.45) | 14.4 (5.7 to 31.8)
Pregnancy
1st trimester | NR | 8.5 (3.1 to 13.9)
2nd trimester | NR | 8.8 (3.8 to 13.8)
3rd trimester | NR | 13.0 (8.4 to 17.6)
Sepsis with multi-organ failure | 0.47 (0.19 to 1.9) | 18.8 (6.3 to 24.1)
Thyroid disease
hypothyroid | 0.38 (0.13 to 0.57) | 11.6 (8.2 to 25)
hyperthyroid | 0.8 (0.68 to 0.97) | 4.5 (3.7 to 5.6)

Note:

In addition to the factors listed above, theophylline clearance is increased and half-life decreased by low carbohydrate/high protein diets, parenteral nutrition, and daily consumption of charcoal-broiled beef. A high carbohydrate/low protein diet can decrease the clearance and prolong the half-life of theophylline.

Absorption:

Theophylline administered in the fed state is completely absorbed after oral administration.

In a single-dose crossover study, two 400 mg theophylline extended-release tablets were administered to19 normal volunteers in the morning or evening immediately following the same standardized meal (769 calories consisting of 97 grams carbohydrates, 33 grams protein and 27 grams fat). There was no evidence of dose dumping nor were there any significant differences in pharmacokinetic parameters attributable to time of drug administration. On the morning arm, the pharmacokinetic parameters were AUC=241.9±83 mcg hr/mL, Cmax=9.3±2 mcg/mL, Tmax=12.8±4.2 hours. On the evening arm, the pharmacokinetic parameters were AUC=219.7±83 mcg hr/mL, Cmax=9.2±2 mcg/mL, Tmax=12.5±4.2 hours.

A study in which theophylline extended-release 400 mg tablets were administered to 17 fed adult asthmatics produced similar theophylline level-time curves when administered in the morning or evening. Serum levels were generally higher in the evening regimen but there were no statistically significant differences between the two regimens.

 | MORNING | EVENING
AUC (0-24 hrs) (mcg hr/mL) | 236 ± 76.7 | 256 ± 80.4
Cmax (mcg/mL) | 14.5 ± 4.1 | 16.3 ± 4.5
Cmin (mcg/mL) | 5.5 ± 2.9 | 5.0 ± 2.5
Tmax (hours) | 8.1 ± 3.7 | 10.1 ± 4.1

A single-dose study in 15 normal fasting male volunteers whose theophylline inherent mean elimination half-life was verified by a liquid theophylline product to be 6.9 ± 2.5 (SD) hours were administered two or three 400 mg theophylline extended-release tablets. The relative bioavailability of theophylline given in the fasting state in comparison to an immediate-release product was 59%. Peak serum theophylline levels occurred at 6.9 ± 5.2 (SD) hours, with a normalized (to 800 mg) peak level being 6.2 ± 2.1 (SD). The apparent elimination half-life for the 400 mg theophylline extended-release tablets was 17.2±5.8 (SD) hours.

Steady-state pharmacokinetics were determined in a study in 12 fasted patients with chronic reversible obstructive pulmonary disease. All were dosed with two 400 mg theophylline extended-release tablets given once daily in the morning and a reference controlled-release BID product administered as two 200 mg tablets given 12 hours apart. The pharmacokinetic parameters obtained for theophylline extended-release tablets given at doses of 800 mg once daily in the morning were virtually identical to the corresponding parameters for the reference drug when given as 400 mg BID. In particular, the AUC, Cmax and Cmin values obtained in this study were as follows:

 | Theophylline Extended-Release Tablets 800 mg Q24h SD | Reference Drug 400 mg Q12h SD
AUC, (0-24 hours), mcg/mL | 288.9 ± 21.5 | 283.5 ± 38.4
Cmax, mcg/mL | 15.7 ± 2.8 | 15.2 ± 2.1
Cmin, mcg/mL | 7.9 ± 1.6 | 7.8 ± 1.7
Cmax-Cmin diff. | 7.7 ± 1.5 | 7.4 ± 1.5

Single-dose studies in which subjects were fasted for twelve (12) hours prior to and an additional four (4) hours following dosing, demonstrated reduced bioavailability as compared to dosing with food. One single-dose study in 20 normal volunteers dosed with two (2) 400 mg tablets in the morning, compared dosing under these fasting conditions with dosing immediately prior to a standardized breakfast (769 calories, consisting of 97 grams carbohydrates, 33 grams protein and 27 grams fat). Under fed conditions, the pharmacokinetic parameters were: AUC=231.7±92.4 mcg hr/mL, Cmax=8.4±2.6 mcg/mL, Tmax=17.3±6.7 hours. Under fasting conditions, these parameters were AUC=141.2±6.53 mcg hr/mL, Cmax=5.5±1.5 mcg/mL, Tmax=6.5±2.1 hours.

Another single-dose study in 21 normal male volunteers, dosed in the evening, compared fasting to a standardized high calorie, high fat meal (870 to 1,020 calories, consisting of 33 grams protein, 55 to 75 grams fat, 58 grams carbohydrates). In the fasting arm subjects received one theophylline extended-release 400mg tablet at 8 p.m. after an eight hour fast followed by a further four hour fast. In the fed arm, subjects were again dosed with one 400 mg theophylline tablet, but at 8 p.m. immediately after the high fat content standardized meal cited above. The pharmacokinetic parameters (normalized to 800 mg) fed were AUC=221.8±40.9 mcg hr/mL, Cmax=10.9±1.7 mcg/mL, Tmax=11.8±2.2 hours. In the fasting arm, the pharmacokinetic parameters (normalized to 800 mg) were AUC=146.4±40.9 mcg hr/mL, Cmax=6.7±1.7 mcg/mL, Tmax=7.3±2.2 hours.

Thus, administration of single theophylline extended-release doses to healthy normal volunteers, under prolonged fasted conditions (at least 10 hour overnight fast before dosing followed by an additional four (4) hour fast after dosing) results in decreased bioavailability. However, there was no failure of this delivery system leading to a sudden and unexpected release of a large quantity of theophylline with theophylline extended-release tablets even when they are administered with a high fat, high calorie meal.

Similar studies were conducted with the 600 mg theophylline extended-release tablet. A single-dose study in 24 subjects with an established theophylline clearance of ≤4 L/hr, compared the pharmacokinetic evaluation of one 600 mg theophylline extended-release tablet and one and one-half 400 mg theophylline extended-release tablets under fed (using a standard high fat diet) and fasted conditions. The results of this 4-way randomized crossover study demonstrate the bioequivalence of the 400 mg and 600 mg theophylline extended-release tablets. Under fed conditions, the pharmacokinetic results for the one and one-half 400 mg tablets were AUC=214.64 ± 55.88 mcg hr/mL, Cmax=10.58 ± 2.21 mcg/mL and Tmax=9 ± 2.64 hours, and for the 600 mg tablet were AUC=207.85 ± 48.9 mcg hr/mL, Cmax=10.39 ± 1.91 mcg/mL and Tmax=9.58 ± 1.86 hours. Under fasted conditions the pharmacokinetic results for the one and one-half 400 mg tablets were AUC=191.85 ± 51.1 mcg hr/mL, Cmax= 7.37 ± 1.83 mcg/mL and Tmax=8.08 ± 4.39 hours; and for the 600 mg tablet were AUC=199.39 ± 70.27 mcg hr/mL, Cmax=7.66 ± 2.09 mcg/mL and Tmax=9.67 ± 4.89 hours.

In this study the mean fed/fasted ratios for the one and one-half 400 mg tablets and the 600 mg tablet were about 112% and 104%, respectively.

In another study, the bioavailability of the 600 mg theophylline extended-release tablet was examined with morning and evening administration. This single-dose, crossover study in 22 healthy males was conducted under fed (standard high fat diet) conditions. The results demonstrated no clinically significant difference in the bioavailability of the 600 mg theophylline extended-release tablet administered in the morning or in the evening. The results were: AUC=233.6 ± 45.1 mcg hr/mL, Cmax=10.6 ± 1.3 mcg/mL and Tmax=12.5 ± 3.2 hours with morning dosing; AUC=209.8 ± 46.2 mcg hr/mL, Cmax=9.7 ± 1.4 mcg/mL and Tmax=13.7 ± 3.3 hours with evening dosing. The PM/AM ratio was 89.3%.

The absorption characteristics of theophylline (anhydrous) extended-release tablets have been extensively studied. A steady-state crossover bioavailability study in 22 normal males compared two theophylline 400 mg tablets administered q24h at 8 a.m. immediately after breakfast with a reference controlled-release theophylline product administered BID in fed subjects at 8 a.m. immediately after breakfast and 8 p.m. immediately after dinner (769 calories, consisting of 97 grams carbohydrates, 33 grams protein and 27 grams fat).

The pharmacokinetic parameters for theophylline 400 mg extended-release tablets under these steady-state conditions were AUC=203.3 ± 87.1 mcg hr/mL, Cmax=12.1 ± 3.8 mcg/mL, Cmin=4.50 ± 3.6, Tmax=8.8 ± 4.6 hours. For the reference BID product, the pharmacokinetic parameters were AUC=219.2 ± 88.4 mcg hr/mL, Cmax=11 ± 4.1 mcg/mL, Cmin=7.28 ± 3.5, Tmax=6.9 ± 3.4 hours. The mean percent fluctuation [(Cmax-Cmin/Cmin)x100]=169% for the once-daily regimen and 51% for the reference product BID regimen.

The bioavailability of the 600 mg theophylline extended-release tablet was further evaluated in a multiple dose, steady-state study in 26 healthy males comparing the 600 mg tablet to one and one-half 400 mg theophylline extended-release tablets. All subjects had previously established theophylline clearances of ≤4 L/hr and were dosed once-daily for 6 days under fed conditions. The results showed no clinically significant difference between the 600 mg and one and one-half 400 mg theophylline extended-release tablet regimens. Steady-state results were:

 | 600 mg Tablet FED | 600 mg (One + One-Half 400 mg Tablets) FED
AUC 0-24 hrs (mcg/mL) | 209.77 ± 51.04 | 212.32 ± 56.29
Cmax (mcg/mL) | 12.91 ± 2.46 | 13.17 ± 3.11
Cmin (mcg/mL) | 5.52 ± 1.79 | 5.39 ± 1.95
Tmax (hours) | 8.62 ± 3.21 | 7.23 ± 2.35
Percent Fluctuation | 183.73 ± 54.02 | 179.72 ± 28.86

The bioavailability ratio for the 600/400 mg tablets was 98.8%. Thus, under all study conditions the 600 mg tablet is bioequivalent to one and one-half 400 mg tablets.

Studies demonstrate that as long as subjects were either consistently fed or consistently fasted, there is similar bioavailability with once-daily administration of theophylline extended-release tablets whether dosed in the morning or evening.

Distribution:

Once theophylline enters the systemic circulation, about 40% is bound to plasma protein, primarily albumin. Unbound theophylline distributes throughout body water, but distributes poorly into body fat. The apparent volume of distribution of theophylline is approximately 0.45 L/kg (range 0.3 to 0.7 L/kg) based on ideal body weight. Theophylline passes freely across the placenta, into breast milk and into the cerebrospinal fluid (CSF). Saliva theophylline concentrations approximate unbound serum concentrations, but are not reliable for routine or therapeutic monitoring unless special techniques are used. An increase in the volume of distribution of theophylline, primarily due to reduction in plasma protein binding, occurs in premature neonates, patients with hepatic cirrhosis, uncorrected acidemia, the elderly and in women during the third trimester of pregnancy. In such cases, the patient may show signs of toxicity at total (bound+unbound) serum concentrations of theophylline in the therapeutic range (10 to 20 mcg/mL) due to elevated concentrations of the pharmacologically active unbound drug. Similarly, a patient with decreased theophylline binding may have a sub-therapeutic total drug concentration while the pharmacologically active unbound concentration is in the therapeutic range. If only total serum theophylline concentration is measured, this may lead to an unnecessary and potentially dangerous dose increase. In patients with reduced protein binding, measurement of unbound serum theophylline concentration provides a more reliable means of dosage adjustment than measurement of total serum theophylline concentration. Generally, concentrations of unbound theophylline should be maintained in the range of 6 to 12 mcg/mL.

Metabolism:

Following oral dosing, theophylline does not undergo any measurable first-pass elimination. In adults and children beyond one year of age, approximately 90% of the dose is metabolized in the liver. Biotransformation takes place through demethylation to 1 methylxanthine and 3-methylxanthine and hydroxylation to 1,3- dimethyluric acid. 1-methylxanthine is further hydroxylated, by xanthine oxidase, to 1-methyluric acid. About 6% of a theophylline dose is N-methylated to caffeine. Theophylline demethylation to 3-methylxanthine is catalyzed by cytochrome P-450 1A2, while cytochromes P-450 2E1 and P-450 3A3 catalyze the hydroxylation to 1,3-dimethyluric acid. Demethylation to 1-methylxanthine appears to be catalyzed either by cytochrome P-450 1A2 or a closely related cytochrome. In neonates, the Ndemethylation pathway is absent while the function of the hydroxylation pathway is markedly deficient. The activity of these pathways slowly increases to maximal levels by one year of age.

Caffeine and 3-methylxanthine are the only theophylline metabolites with pharmacologic activity. 3-methylxanthine has approximately one tenth the pharmacologic activity of theophylline and serum concentrations in adults with normal renal function are <1 mcg/mL. In patients with end-stage renal disease, 3-methylxanthine may accumulate to concentrations that approximate the unmetabolized theophylline concentration. Caffeine concentrations are usually undetectable in adults regardless of renal function. In neonates, caffeine may accumulate to concentrations that approximate the unmetabolized theophylline concentration and thus, exert a pharmacologic effect.

Both the N-demethylation and hydroxylation pathways of theophylline biotransformation are capacity-limited. Due to the wide intersubject variability of the rate of theophylline metabolism, non-linearity of elimination may begin in some patients at serum theophylline concentrations <10 mcg/mL. Since this non-linearity results in more than proportional changes in serum theophylline concentrations with changes in dose, it is advisable to make increases or decreases in dose in small increments in order to achieve desired changes in serum theophylline concentrations (see DOSAGE AND ADMINISTRATION, Table VI). Accurate prediction of dosedependency of theophylline metabolism in patients a priori is not possible, but patients with very high initial clearance rates (i.e., low steady-state serum theophylline concentrations at above average doses) have the greatest likelihood of experiencing large changes in serum theophylline concentration in response to dosage changes.

Excretion:

In neonates, approximately 50% of the theophylline dose is excreted unchanged in the urine. Beyond the first three months of life, approximately 10% of the theophylline dose is excreted unchanged in the urine. The remainder is excreted in the urine mainly as 1,3-dimethyluric acid (35 to 40%), 1-methyluric acid (20 to 25%) and 3-methylxanthine (15 to 20%). Since little theophylline is excreted unchanged in the urine and since active metabolites of theophylline (i.e., caffeine, 3-methylxanthine) do not accumulate to clinically significant levels even in the face of end-stage renal disease, no dosage adjustment for renal insufficiency is necessary in adults and children >3 months of age. In contrast, the large fraction of the theophylline dose excreted in the urine as unchanged theophylline and caffeine in neonates requires careful attention to dose reduction and frequent monitoring of serum theophylline concentrations in neonates with reduced renal function (See WARNINGS).

Serum Concentrations at Steady-State:

After multiple doses of theophylline, steady-state is reached in 30 to 65 hours (average 40 hours) in adults. At steady-state, on a dosage regimen with 24-hour intervals, the expected mean trough concentration is approximately 50% of the mean peak concentration, assuming a mean theophylline half-life of 8 hours. The difference between peak and trough concentrations is larger in patients with more rapid theophylline clearance. In these patients administration of theophylline may be required more frequently (every 12 hours).

Special Populations (See Table I for mean clearance and half-life values).

Geriatric:

The clearance of theophylline is decreased by an average of 30% in healthy elderly adults (>60 yrs) compared to healthy young adults. Careful attention to dose reduction and frequent monitoring of serum theophylline concentrations are required in elderly patients (see WARNINGS).

Pediatrics:

The clearance of theophylline is very low in neonates (see WARNINGS). Theophylline clearance reaches maximal values by one year of age, remains relatively constant until about 9 years of age and then slowly decreases by approximately 50% to adult values at about age 16. Renal excretion of unchanged theophylline in neonates amounts to about 50% of the dose, compared to about 10% in children older than three months and in adults. Careful attention to dosage selection and monitoring of serum theophylline concentrations are required in pediatric patients (see WARNINGS and DOSAGE ANDADMINISTRATION).

Gender:

Gender differences in theophylline clearance are relatively small and unlikely to be of clinical significance. Significant reduction in theophylline clearance, however, has been reported in women on the 20th day of the menstrual cycle and during the third trimester of pregnancy.

Race:

Pharmacokinetic differences in theophylline clearance due to race have not been studied.

Renal Insufficiency:

Only a small fraction, e.g., about 10%, of the administered theophylline dose is excreted unchanged in the urine of children greater than three months of age and adults. Since little theophylline is excreted unchanged in the urine and since active metabolites of theophylline (i.e., caffeine, 3-methylxanthine) do not accumulate to clinically significant levels even in the face of end-stage renal disease, no dosage adjustment for renal insufficiency is necessary in adults and children >3 months of age. In contrast, approximately 50% of the administered theophylline dose is excreted unchanged in the urine in neonates. Careful attention to dose reduction and frequent monitoring of serum theophylline concentrations are required in neonates with decreased renal function (see WARNINGS).

Hepatic Insufficiency:

Theophylline clearance is decreased by 50% or more in patients with hepatic insufficiency (e.g., cirrhosis, acute hepatitis, cholestasis). Careful attention to dose reduction and frequent monitoring of serum theophylline concentrations are required in patients with reduced hepatic function (see WARNINGS).

Congestive Heart Failure (CHF):

Theophylline clearance is decreased by 50% or more in patients with CHF. The extent of reduction in theophylline clearance in patients with CHF appears to be directly correlated to the severity of the cardiac disease. Since theophylline clearance is independent of liver blood flow, the reduction in clearance appears to be due to impaired hepatocyte function rather than reduced perfusion. Careful attention to dose reduction and frequent monitoring of serum theophylline concentrations are required in patients with CHF (see WARNINGS).

Smokers:

Tobacco and marijuana smoking appears to increase the clearance of theophylline by induction of metabolic pathways. Theophylline clearance has been shown to increase by approximately 50% in young adult tobacco smokers and by approximately 80% in elderly tobacco smokers compared to non-smoking subjects. Passive smoke exposure has also been shown to increase theophylline clearance by up to 50%. Abstinence from tobacco smoking for one week causes a reduction of approximately 40% in theophylline clearance. Careful attention to dose reduction and frequent monitoring of serum theophylline concentrations are required in patients who stop smoking (see WARNINGS). Use of nicotine gum has been shown to have no effect on theophylline clearance.

Fever:

Fever, regardless of its underlying cause, can decrease the clearance of theophylline. The magnitude and duration of the fever appear to be directly correlated to the degree of decrease of theophylline clearance. Precise data are lacking, but a temperature of 39°C (102°F) for at least 24 hours is probably required to produce a clinically significant increase in serum theophylline concentrations. Children with rapid rates of theophylline clearance (i.e., those who require a dose that is substantially larger than average [e.g., >22 mg/kg/day] to achieve a therapeutic peak serum theophylline concentration when afebrile) may be at greater risk of toxic effects from decreased clearance during sustained fever. Careful attention to dose reduction and frequent monitoring of serum theophylline concentrations are required in patients with sustained fever (see WARNINGS).

Miscellaneous:

Other factors associated with decreased theophylline clearance include the third trimester of pregnancy, sepsis with multiple organ failure, and hypothyroidism. Careful attention to dose reduction and frequent monitoring of serum theophylline concentrations are required in patients with any of these conditions (see WARNINGS). Other factors associated with increased theophylline clearance include hyperthyroidism and cystic fibrosis.

Clinical Studies

In patients with chronic asthma, including patients with severe asthma requiring inhaled corticosteroids or alternate-day oral corticosteroids, many clinical studies have shown that theophylline decreases the frequency and severity of symptoms, including nocturnal exacerbations, and decreases the “as needed” use of inhaled beta-2 agonists. Theophylline has also been shown to reduce the need for short courses of daily oral prednisone to relieve exacerbations of airway obstruction that are unresponsive to bronchodilators in asthmatics.

In patients with chronic obstructive pulmonary disease (COPD), clinical studies have shown that theophylline decreases dyspnea, air trapping, the work of breathing, and improves contractility of diaphragmatic muscles with little or no improvement in pulmonary function measurements.

INDICATIONS AND USAGE

Theophylline is indicated for the treatment of the symptoms and reversible airflow obstruction associated with chronic asthma and other chronic lung diseases, e.g., emphysema and chronic bronchitis.

CONTRAINDICATIONS

Theophylline extended-release tablets are contraindicated in patients with a history of hypersensitivity to theophylline or other components in the product.

WARNINGS

Concurrent Illness

Theophylline should be used with extreme caution in patients with the following clinical conditions due to the increased risk of exacerbation of the concurrent condition:

Active peptic ulcer disease
Seizure disorders
Cardiac arrhythmias (not including bradyarrhythmias)

Conditions That Reduce Theophylline Clearance

There are several readily identifiable causes of reduced theophylline clearance. If the total daily dose is not appropriately reduced in the presence of these risk factors, severe and potentially fatal theophylline toxicity can occur. Careful consideration must be given to the benefits and risks of theophylline use and the need for more intensive monitoring of serum theophylline concentrations in patients with the following risk factors:

Age

Neonates (term and premature)
Children <1 year
Elderly (>60 years)

Concurrent Diseases

Acute pulmonary edema
Congestive heart failure
Cor-pulmonale
Fever; ≥102° for 24 hours or more; or lesser temperature elevations for longer periods
Hypothyroidism
Liver disease; cirrhosis, acute hepatitis
Reduced renal function in infants <3 months of age
Sepsis with multi-organ failure
Shock

Cessation of Smoking

Drug Interactions:

Adding a drug that inhibits theophylline metabolism (e.g., cimetidine, erythromycin, tacrine) or stopping a concurrently administered drug that enhances theophylline metabolism (e.g., carbamazepine, rifampin). (See PRECAUTIONS, Drug Interactions, Table II).

When Signs or Symptoms of Theophylline Toxicity Are Present

Whenever a patient receiving theophylline develops nausea or vomiting, particularly repetitive vomiting, or other signs or symptoms consistent with theophylline toxicity (even if another cause may be suspected), additional doses of theophylline should be withheld and a serum theophylline concentration measured immediately. Patients should be instructed not to continue any dosage that causes adverse effects and to withhold subsequent doses until the symptoms have resolved, at which time the healthcare professional may instruct the patient to resume the drug at a lower dosage (see DOSAGE AND ADMINISTRATION, Dosing Guidelines, Table VI).

Dosage Increases

Increases in the dose of theophylline should not be made in response to an acute exacerbation of symptoms of chronic lung disease since theophylline provides little added benefit to inhaled beta2-selective agonists and systemically administered corticosteroids in this circumstance and increases the risk of adverse effects. A peak steady-state serum theophylline concentration should be measured before increasing the dose in response to persistent chronic symptoms to ascertain whether an increase in dose is safe. Before increasing the theophylline dose on the basis of a low serum concentration, the healthcare professional should consider whether the blood sample was obtained at an appropriate time in relationship to the dose and whether the patient has adhered to the prescribed regimen (see PRECAUTIONS, Laboratory Tests).

As the rate of theophylline clearance may be dose-dependent (i.e., steady-state serum concentrations may increase disproportionately to the increase in dose), an increase in dose based upon a sub-therapeutic serum concentration measurement should be conservative. In general, limiting dose increases to about 25% of the previous total daily dose will reduce the risk of unintended excessive increases in serum theophylline concentration (see DOSAGE AND ADMINISTRATION, Table VI).

PRECAUTIONS

General

Careful consideration of the various interacting drugs and physiologic conditions that can alter theophylline clearance and require dosage adjustment should occur prior to initiation of theophylline therapy, prior to increases in theophylline dose, and during follow up (see WARNINGS). The dose of theophylline selected for initiation of therapy should be low and, if tolerated, increased slowly over a period of a week or longer with the final dose guided by monitoring serum theophylline concentrations and the patient’s clinical response (see DOSAGE AND ADMINISTRATION, Table V).

Monitoring Serum Theophylline Concentrations

Serum theophylline concentration measurements are readily available and should be used to determine whether the dosage is appropriate. Specifically, the serum theophylline concentration should be measured as follows:

- When initiating therapy to guide final dosage adjustment after titration.
- Before making a dose increase to determine whether the serum concentration is sub-therapeutic in a patient who continues to be symptomatic.
- Whenever signs or symptoms of theophylline toxicity are present.
- Whenever there is a new illness, worsening of a chronic illness or a change in the patient’s treatment regimen that may alter theophylline clearance (e.g., fever >102°F sustained for ≥24 hours, hepatitis, or drugs listed in Table II are added or discontinued).

To guide a dose increase, the blood sample should be obtained at the time of the expected peak serum theophylline concentration; 12 hours after an evening dose or 9 hours after a morning dose at steady-state. For most patients, steady-state will be reached after 3 days of dosing when no doses have been missed, no extra doses have been added, and none of the doses have been taken at unequal intervals. A trough concentration (i.e., at the end of the dosing interval) provides no additional useful information and may lead to an inappropriate dose increase since the peak serum theophylline concentration can be two or more times greater than the trough concentration with an immediate-release formulation. If the serum sample is drawn more than 12 hours after the evening dose, or more than 9 hours after a morning dose, the results must be interpreted with caution since the concentration may not be reflective of the peak concentration. In contrast, when signs or symptoms of theophylline toxicity are present, a serum sample should be obtained as soon as possible, analyzed immediately, and the result reported to the healthcare professional without delay. In patients in whom decreased serum protein binding is suspected (e.g., cirrhosis, women during the third trimester of pregnancy), the concentration of unbound theophylline should be measured and the dosage adjusted to achieve an unbound concentration of 6 to 12 mcg/mL.

Saliva concentrations of theophylline cannot be used reliably to adjust dosage without special techniques.

Effects on Laboratory Tests

As a result of its pharmacological effects, theophylline at serum concentrations within the 10 to 20 mcg/mL range modestly increases plasma glucose (from a mean of 88 mg% to 98 mg%), uric acid (from a mean of 4 mg/dL to 6 mg/dL), free fatty acids (from a mean of 451 μEq/L to 800 μEq/L, total cholesterol (from a mean of 140 vs 160 mg/dL), HDL (from a mean of 36 to 50 mg/dL), HDL/LDL ratio (from a mean of 0.5 to 0.7), and urinary free cortisol excretion (from a mean of 44 to 63 mcg/24 hr). Theophylline at serum concentrations within the 10 to 20 mcg/mL range may also transiently decrease serum concentrations of triiodothyronine (144 before, 131 after one week and 142 ng/dL after 4 weeks of theophylline). The clinical importance of these changes should be weighed against the potential therapeutic benefit of theophylline in individual patients.

Information for Patients:

The patient (or parent/caregiver) should be instructed to seek medical advice whenever nausea, vomiting, persistent headache, insomnia, or rapid heartbeat occurs during treatment with theophylline, even if another cause is supected. The patient should be instructed to contact their healthcare professional if they develop a new illness, especially if accompanied by a persistent fever, if they experience worsening of a chronic illness, if they start or stop smoking cigarettes or marijuana, or if another healthcare professional adds a new medication or discontinues a previously prescribed medication. Patients should be informed that theophylline interacts with a wide variety of drugs (see Table II). The dietary supplement St.John's Wort (Hypericum perforatum) should not be taken at the same time as theophylline, since it may result in decreased theophylline levels. If patients are already taking St. John's Wort and theophylline together, they should consult their healthcare professional before stopping the St. John's Wort, since their theophylline concentrations may rise when this is done, resulting in toxicity. Patients should be instructed to inform all healthcare professionals involved in their care that they are taking theophylline, especially when a medication is being added or deleted from their treatment. Patients should be instructed to not alter the dose, timing of the dose, or frequency of administration without first consulting their healthcare professional. If a dose is missed, the patient should be instructed to take the next dose at the usually scheduled time and to not attempt to make up for the missed dose.

Theophylline tablets can be taken once a day in the morning or evening. It is recommended that theophylline be taken with meals. Patients should be advised that if they choose to take theophylline with food it should be taken consistently with food and if they take it in a fasted condition it should routinely be taken fasted. It is important that the product whenever dosed be dosed consistently with or without food.

Theophylline tablets are not to be chewed or crushed because it may lead to a rapid release of theophylline with the potential for toxicity. The scored tablet may be split. Patients receiving theophylline tablets may pass an intact matrix tablet in the stool or via colostomy. These matrix tablets usually contain little or no residual theophylline.

Drug Interactions

Theophylline interacts with a wide variety of drugs. The interaction may be pharmacodynamic, i.e., alterations in the therapeutic response to theophylline or another drug or occurrence of adverse effects without a change in serum theophylline concentration. More frequently, however, the interaction is pharmacokinetic, i.e., the rate of theophylline clearance is altered by another drug resulting in increased or decreased serum theophylline concentrations. Theophylline only rarely alters the pharmacokinetics of other drugs.

The drugs listed in Table II have the potential to produce clinically significant pharmacodynamic or pharmacokinetic interactions with theophylline. The information in the “Effect” column of Table II assumes that the interacting drug is being added to a steady-state theophylline regimen. If theophylline is being initiated in a patient who is already taking a drug that inhibits theophylline clearance (e.g., cimetidine, erythromycin), the dose of theophylline required to achieve a therapeutic serum theophylline concentration will be smaller. Conversely, if theophylline is being initiated in a patient who is already taking a drug that enhances theophylline clearance (e.g., rifampin), the dose of theophylline required to achieve a therapeutic serum theophylline concentration will be larger. Discontinuation of a concomitant drug that increases theophylline clearance will result in accumulation of theophylline to potentially toxic levels, unless the theophylline dose is appropriately reduced. Discontinuation of a concomitant drug that inhibits theophylline clearance will result in decreased serum theophylline concentrations, unless the theophylline dose is appropriately increased.

The drugs listed in Table III have either been documented not to interact with theophylline or do not produce a clinically significant interaction (i.e., <15% change in theophylline clearance).

The listing of drugs in Tables II and III are current as of February 9, 1995. New interactions are continuously being reported for theophylline, especially with new chemical entities. The healthcare professional should not assume that a drug does not interact with theophylline if it is not listed in Table II. Before addition of a newly available drug in a patient receiving theophylline, the package insert of the new drug and/or the medical literature should be consulted to determine if an interaction between the new drug and theophylline has been reported.

Table II. Clinically significant drug interactions with theophylline. [*Refer to PRECAUTIONS, Drug Interactions for further information regarding table.]
Drug | Type of Interaction | Effect [Average effect on steady-state theophylline concentration or other clinical effect for pharmacologic interactions. Individual patients may experience larger changes in serum theophylline concentration than the value listed.]
Adenosine | Theophylline blocks adenosine receptors. | Higher doses of adenosine may be required to achieve desired effect.
Alcohol | A single large dose of alcohol (3 mL/kg of whiskey) decreases theophylline clearance for up to 24 hours. | 30% increase
Allopurinol | Decreases theophylline clearance at allopurinol doses > 600 mg/day. | 25% increase
Aminoglutethimide | Increases theophylline clearance by induction of microsomal enzyme activity. | 25% decrease
Carbamazepine | Similar to aminoglutethimide. | 30% decrease
Cimetidine | Decreases theophylline clearance by inhibiting cytochrome P450 1A2. | 70% increase
Ciprofloxacin | Similar to cimetidine. | 40% increase
Clarithromycin | Similar to erythromycin. | 25% increase
Diazepam | Benzodiazepines increase CNS concentrations of adenosine, a potent CNS depressant, while theophylline blocks adenosine receptors. | Larger diazepam doses may be required to produce desired level of sedation. Discontinuation of theophylline without reduction of diazepam dose may result in respiratory depression.
Disulfiram | Decreases theophylline clearance by inhibiting hydroxylation and demethylation. | 50% increase
Enoxacin | Similar to cimetidine. | 300% increase
Ephedrine | Synergistic CNS effects. | Increased frequency of nausea, nervousness, and insomnia.
Erythromycin | Erythromycin metabolite decreases theophylline clearance by inhibiting cytochrome P450 3A3. | 35% increase. Erythromycin steady-state serum concentrations decrease by a similar amount.
Estrogen | Estrogen containing oral contraceptives decrease theophylline clearance in a dose-dependent fashion. The effect of progesterone on theophylline clearance is unknown. | 30% increase.
Flurazepam | Similar to diazepam. | Similar to diazepam.
Fluvoxamine | Similar to cimetidine. | Similar to cimetidine.
Halothane | Halothane sensitizes the myocardium to catecholamines, theophylline increases release of endogenous catecholamines. | Increased risk of ventricular arrhythmias.
Interferon, human recombinant alpha-A | Decreases theophylline clearance. | 100% increase
Isoproterenol (IV) | Increases theophylline clearance. | 20% decrease
Ketamine | Pharmacologic | May lower theophylline seizure threshold.
Lithium | Theophylline increases renal lithium clearance. | Lithium dose required to achieve a therapeutic serum concentration increased an average of 60%.
Lorazepam | Similar to diazepam. | Similar to diazepam.
Methotrexate (MTX) | Decreases theophylline clearance. | 20% increase after low dose MTX, higher dose MTX may have a greater effect.
Mexiletine | Similar to disulfiram. | 80% increase
Midazolam | Similar to diazepam. | Similar to diazepam.
Moricizine | Increases theophylline clearance. | 25% decrease
Pancuronium | Theophylline may antagonize non-depolarizing neuromuscular blocking effects, possibly due to phosphodiesterase inhibition. | Larger dose of pancuronium may be required to achieve neuromuscular blockade.
Pentoxifylline | Decreases theophylline clearance. | 30% increase
Phenobarbital (PB) | Similar to aminoglutethimide. | 25% decrease after two weeks of concurrent PB.
Phenytoin | Phenytoin increases theophylline clearance by increasing microsomal enzyme activity. Theophylline decreases phenytoin absorption. | Serum theophylline and phenytoin concentrations decrease about 40%.
Propafenone | Decreases theophylline clearance and pharmacologic interaction. | 40% increase. Beta-2 blocking effect may decrease efficacy of theophylline.
Propranolol | Similar to cimetidine and pharmacologic interaction. | 100% increase. Beta-2 blocking effect may decrease efficacy of theophylline.
Rifampin | Increases theophylline clearance by increasing cytochrome P450 1A2 and 3A3 activity. | 20 to 40% decrease.
St. John's Wort (Hypericum Perforatum) | Decrease in theophylline plasma concentrations. | Higher doses of theophylline may be required to achieve desired effect. Stopping St. John's Wort may result in theophylline toxicity.
Sulfinpyrazone | Increases theophylline clearance by increasing demethylation and hydroxylation. Decreases renal clearance of theophylline. | 20% decrease
Tacrine | Similar to cimetidine, also increases renal clearance of theophylline. | 90% increase
Thiabendazole | Decreases theophylline clearance. | 190% increase
Ticlopidine | Decreases theophylline clearance. | 60% increase
Troleandomycin | Similar to erythromycin. | 33 to 100% increase depending on troleandomycin dose.
Verapamil | Similar to disulfiram. | 20% increase

Table III. Drugs that have been documented not to interact with theophylline or drugs that produce no clinically significant interaction with theophylline. [Refer to PRECAUTIONS, Drug Interactions for information regarding table.]
albuterol, systemic and inhaled | mebendazole
amoxicillin | medroxyprogesterone
ampicillin, with or without sulbactam | methylprednisolone
atenolol | metronidazole
azithromycin | metoprolol
caffeine, dietary ingestion | nadolol
cefaclor | nifedipine
co-trimoxazole (trimethoprim and sulfamethoxazole) | nizatidine
diltiazem | norfloxacin
dirithromycin | ofloxacin
enflurane | omeprazole
famotidine | prednisone, prednisolone
felodipine | ranitidine
finasteride | rifabutin
hydrocortisone | roxithromycin
isoflurane | sorbitol (purgative doses do not inhibit theophylline absorption)
isoniazid | sucralfate
isradipine | terbutaline, systemic
influenza vaccine | terfenadine
ketoconazole | tetracycline
lomefloxacin | tocainide

Drug-Food Interactions:

The bioavailability of theophylline (anhydrous) tablets has been studied with co-administration of food. In three single-dose studies, subjects given theophylline 400 mg or 600 mg tablets with a standardized high-fat meal were compared to fasted conditions. Under fed conditions, the peak plasma concentration and bioavailability were increased; however, a precipitous increase in the rate and extent of absorption was not evident (see Pharmacokinetics, Absorption). The increased peak and extent of absorption under fed conditions suggests that dosing should be ideally administered consistently either with or without food.

The Effect of Other Drugs on Theophylline Serum Concentration Measurements:

Most serum theophylline assays in clinical use are immunoassays which are specific for theophylline. Other xanthines such as caffeine, dyphylline, and pentoxifylline are not detected by these assays. Some drugs (e.g., cefazolin, cephalothin), however, may interfere with certain HPLC techniques. Caffeine and xanthine metabolites in neonates or patients with renal dysfunction may cause the reading from some dry reagent office methods to be higher than the actual serum theophylline concentration.

Carcinogenesis, Mutagenesis, and Impairment of Fertility:

Long term carcinogenicity studies have been carried out in mice (oral doses 30 to 150 mg/kg) and rats (oral doses 5 to 75 mg/kg). Results are pending.

Theophylline has been studied in Ames salmonella, in vivo and in vitro cytogenetics, micronucleus and Chinese hamster ovary test systems and has not been shown to be genotoxic.

In a 14 week continuous breeding study, theophylline, administered to mating pairs of B6C3F1mice at oral doses of 120, 270 and 500 mg/kg (approximately 1 to 3 times the human dose on a mg/m^2basis) impaired fertility, as evidenced by decreases in the number of live pups per litter, decreases in the mean number of litters per fertile pair, and increases in the gestation period at the high dose as well as decreases in the proportion of pups born alive at the mid and high dose. In 13 week toxicity studies, theophylline was administered to F344 rats and B6C3F1mice at oral doses of 40 to 300 mg/kg (approximately 2 times the human dose on a mg/m^2basis). At the high dose, systemic toxicity was observed in both species including decreases in testicular weight.

Pregnancy: Teratogenic Effects: Category C

In studies in which pregnant mice, rats and rabbits were dosed during the period of organogenesis, theophylline produced teratogenic effects.

In studies with mice, a single intraperitoneal dose at and above 100 mg/kg (approximately equal to the maximum recommended oral dose for adults on a mg/m^2 basis) during organogenesis produced cleft palate and digital abnormalities. Micromelia, micrognathia, clubfoot, subcutaneous hematoma, open eyelids, and embryolethality were observed at doses that are approximately 2 times the maximum recommended oral dose for adults on a mg/m^2 basis.

In a study with rats dosed from conception through organogenesis, an oral dose of 150 mg/kg/day (approximately 2 times the maximum recommended oral dose for adults on a mg/m^2 basis) produced digital abnormalities. Embryolethality was observed with a subcutaneous dose of 200 mg/kg/day (approximately 4 times the maximum recommended oral dose for adults on a mg/m^2 basis).

In a study in which pregnant rabbits were dosed throughout organogenesis, an intravenous dose of 60 mg/kg/day (approximately 2 times the maximum recommended oral dose for adults on a mg/m^2 basis), which caused the death of one doe and clinical signs in others, produced cleft palate and was embryolethal. Doses at and above 15 mg/kg/day (less than the maximum recommended oral dose for adults on a mg/m^2 basis) increased the incidence of skeletal variations.

There are no adequate and well-controlled studies in pregnant women. Theophylline should be used during pregnancy only if the potential benefit justifies the potential risk to the fetus.

Nursing Mothers:

Theophylline is excreted into breast milk and may cause irritability or other signs of mild toxicity in nursing human infants. The concentration of theophylline in breast milk is about equivalent to the maternal serum concentration. An infant ingesting a liter of breast milk containing 10 to 20 mcg/mL of theophylline per day is likely to receive 10 to 20 mg of theophylline per day. Serious adverse effects in the infant are unlikely unless the mother has toxic serum theophylline concentrations.

Pediatric Use:

Theophylline is safe and effective for the approved indications in pediatric patients. The maintenance dose of theophylline must be selected with caution in pediatric patients since the rate of theophylline clearance is highly variable across the pediatric age range (see CLINICAL PHARMACOLOGY, Table I, WARNINGS, and DOSAGE AND ADMINISTRATION, Table V).

Geriatric Use:

Elderly patients are at a significantly greater risk of experiencing serious toxicity from theophylline than younger patients due to pharmacokinetic and pharmacodynamic changes associated with aging. The clearance of theophylline is decreased by an average of 30% in healthy elderly adults (>60 yrs) compared to healthy young adults. Theophylline clearance may be further reduced by concomitant diseases prevalent in the elderly, which further impair clearance of this drug and have the potential to increase serum levels and potential toxicity. These conditions include impaired renal function, chronic obstructive pulmonary disease, congestive heart failure, hepatic disease and an increased prevalence of use of certain medications (see PRECAUTIONS: Drug Interactions) with the potential for pharmacokinetic and pharmacodynamic interaction. Protein binding may be decreased in the elderly resulting in an increased proportion of the total serum theophylline concentration in the pharmacologically active unbound form. Elderly patients also appear to be more sensitive to the toxic effects of theophylline after chronic overdosage than younger patients. Careful attention to dose reduction and frequent monitoring of serum theophylline concentrations are required in elderly patients (see PRECAUTIONS, Monitoring Serum Theophylline Concentrations, and DOSAGE AND ADMINISTRATION). The maximum daily dose of theophylline in patients greater than 60 years of age ordinarily should not exceed 400 mg/day unless the patient continues to be symptomatic and the peak steady-state serum theophylline concentration is <10 mcg/mL (see DOSAGE AND ADMINISTRATION). Theophylline doses greater than 400 mg/d should be prescribed with caution in elderly patients.

ADVERSE REACTIONS

Adverse reactions associated with theophylline are generally mild when peak serum theophylline concentrations are <20 mcg/mL and mainly consist of transient caffeine-like adverse effects such as nausea, vomiting, headache, and insomnia. When peak serum theophylline concentrations exceed 20 mcg/mL, however, theophylline produces a wide range of adverse reactions including persistent vomiting, cardiac arrhythmias, and intractable seizures which can be lethal (see OVERDOSAGE). The transient caffeine-like adverse reactions occur in about 50% of patients when theophylline therapy is initiated at doses higher than recommended initial doses (e.g., >300 mg/day in adults and >12 mg/kg/day in children beyond >1 year of age). During the initiation of theophylline therapy, caffeine-like adverse effects may transiently alter patient behavior, especially in school age children, but this response rarely persists. Initiation of theophylline therapy at a low dose with subsequent slow titration to a predetermined age-related maximum dose will significantly reduce the frequency of these transient adverse effects (see DOSAGE AND ADMINISTRATION, Table V). In a small percentage of patients (<3% of children and <10% of adults) the caffeine-like adverse effects persist during maintenance therapy, even at peak serum theophylline concentrations within the therapeutic range (i.e., 10 to 20 mcg/mL). Dosage reduction may alleviate the caffeine-like adverse effects in these patients, however, persistent adverse effects should result in a reevaluation of the need for continued theophylline therapy and the potential therapeutic benefit of alternative treatment.

Other adverse reactions that have been reported at serum theophylline concentrations <20 mcg/mL include diarrhea, irritability, restlessness, fine skeletal muscle tremors, and transient diuresis. In patients with hypoxia secondary to COPD, multifocal atrial tachycardia and flutter have been reported at serum theophylline concentrations ≥15 mcg/mL. There have been a few isolated reports of seizures at serum theophylline concentrations <20 mcg/mL in patients with an underlying neurological disease or in elderly patients. The occurrence of seizures in elderly patients with serum theophylline concentrations <20 mcg/mL may be secondary to decreased protein binding resulting in a larger proportion of the total serum theophylline concentration in the pharmacologically active unbound form. The clinical characteristics of the seizures reported in patients with serum theophylline concentrations <20 mcg/mL have generally been milder than seizures associated with excessive serum theophylline concentrations resulting from an overdose (i.e., they have generally been transient, often stopped without anticonvulsant therapy, and did not result in neurological residua).

Table IV. Manifestations of theophylline toxicity. [These data are derived from two studies in patients with serum theophylline concentrations >30 mcg/mL. In the first study (Study #1—Shanon, Ann Intern Med 1993;119:1161-67), data were prospectively collected from 249 consecutive cases of theophylline toxicity referred to a regional poison center for consultation. In the second study (Study #2—Sessler, Am J Med 1990;88:567-76), data were retrospectively collected from 116 cases with serum theophylline concentrations >30 mcg/mL among 6000 blood samples obtained for measurement of serum theophylline concentrations in three emergency departments. Differences in the incidence of manifestations of theophylline toxicity between the two studies may reflect sample selection as a result of study design (e.g., in Study #1, 48% of the patients had acute intoxications versus only 10% in Study #2) and different methods of reporting results.]
 | Percentage of patients reported with sign or symptom
 | Acute Overdose (Large Single Ingestion) |  | Chronic Overdosage (Multiple Excessive Doses)
Sign/Symptom | Study 1 (n = 157) | Study 2 (n = 14) | Study 1 (n = 92) | Study 2 (n = 102)
Asymptomatic | NR ** | 0 | NR ** | 6
Gastrointestinal Vomiting Abdominal Pain Diarrhea Hematemesis | 73 NR** NR** NR** | 93 21 0 0 | 30 NR** NR** NR** | 61 12 14 2
Metabolic/Other Hypokalemia Hyperglycemia Acid/base disturbance Rhabdomyolysis | 85 98 34 NR** | 79 NR** 21 7 | 44 18 9 NR** | 43 NR** 5 0
Cardiovascular Sinus tachycardia Other supraventricular tachycardias Ventricular premature beats Atrial fibrillation or flutter Multifocal atrial tachycardia Ventricular arrhythmias with hemodynamic instability Hypotension/shock | 100 2 3 1 0 7 NR** | 86 21 21 NR** NR** 14 21 | 100 12 10 12 2 40 NR** | 62 14 19 NR** NR** 0 8
Neurologic Nervousness Tremors Disorientation Seizures | NR** 38 NR** 5 | 64 29 7 14 | NR** 16 NR** 14 | 21 14 11 5
Death | 3 | 21 | 10 | 4
**NR=Not reported in a comparable manner.

OVERDOSAGE

General

The chronicity and pattern of theophylline overdosage significantly influences clinical manifestations of toxicity, management and outcome. There are two common presentations: (1) acute overdose, i.e., ingestion of a single large excessive dose (>10 mg/kg), as occurs in the context of an attempted suicide or isolated medication error, and (2) chronic overdosage, i.e., ingestion of repeated doses that are excessive for the patient’s rate of theophylline clearance. The most common causes of chronic theophylline overdosage include patient or caregiver error in dosing, healthcare professional prescribing of an excessive dose or a normal dose in the presence of factors known to decrease the rate of theophylline clearance, and increasing the dose in response to an exacerbation of symptoms without first measuring the serum theophylline concentration to determine whether a dose increase is safe.

Severe toxicity from theophylline overdose is a relatively rare event. In one health maintenance organization, the frequency of hospital admissions for chronic overdosage of theophylline was about 1 per 1000 person-years exposure. In another study, among 6000 blood samples obtained for measurement of serum theophylline concentration, for any reason, from patients treated in an emergency department, 7% were in the 20 to 30 mcg/mL range and 3% were >30 mcg/mL. Approximately two-thirds of the patients with serum theophylline concentrations in the 20 to 30 mcg/mL range had one or more manifestations of toxicity while >90% of patients with serum theophylline concentrations >30 mcg/mL were clinically intoxicated. Similarly, in other reports, serious toxicity from theophylline is seen principally at serum concentrations >30 mcg/mL.

Several studies have described the clinical manifestations of theophylline overdose and attempted to determine the factors that predict life-threatening toxicity. In general, patients who experience an acute overdose are less likely to experience seizures than patients who have experienced a chronic overdosage, unless the peak serum theophylline concentration is >100 mcg/mL. After a chronic overdosage, generalized seizures, life-threatening cardiac arrhythmias, and death may occur at serum theophylline concentrations >30 mcg/mL. The severity of toxicity after chronic overdosage is more strongly correlated with the patient’s age than the peak serum theophylline concentration; patients >60 years are at the greatest risk for severe toxicity and mortality after a chronic overdosage. Pre-existing or concurrent disease may also significantly increase the susceptibility of a patient to a particular toxic manifestation, e.g., patients with neurologic disorders have an increased risk of seizures and patients with cardiac disease have an increased risk of cardiac arrhythmias for a given serum theophylline concentration compared to patients without the underlying disease.

The frequency of various reported manifestations of theophylline overdose according to the mode of overdose are listed in Table IV.

Other manifestations of theophylline toxicity include increases in serum calcium, creatine kinase, myoglobin and leukocyte count, decreases in serum phosphate and magnesium, acute myocardial infarction, and urinary retention in men with obstructive uropathy.

Seizures associated with serum theophylline concentrations >30 mcg/mL are often resistant to anticonvulsant therapy and may result in irreversible brain injury if not rapidly controlled. Death from theophylline toxicity is most often secondary to cardiorespiratory arrest and/or hypoxic encephalopathy following prolonged generalized seizures or intractable cardiac arrhythmias causing hemodynamic compromise.

Overdose Management

General Recommendations for Patients with Symptoms of Theophylline Overdose or Serum Theophylline Concentrations >30 mcg/mL (Note: Serum theophylline concentrations may continue to increase after presentation of the patient for medical care.)

1. While simultaneously instituting treatment, contact a regional poison center to obtain updated information and advice on individualizing the recommendations that follow.
2. Institute supportive care, including establishment of intravenous access, maintenance of the airway, and electrocardiographic monitoring.
3. Treatment of seizures Because of the high morbidity and mortality associated with theophylline-induced seizures, treatment should be rapid and aggressive. Anticonvulsant therapy should be initiated with an intravenous benzodiazepine, e.g., diazepam, in increments of 0.1 to 0.2 mg/kg every 1 to 3 minutes until seizures are terminated. Repetitive seizures should be treated with a loading dose of phenobarbital (20 mg/kg infused over 30 to 60 minutes). Case reports of theophylline overdose in humans and animal studies suggest that phenytoin is ineffective in terminating theophylline-induced seizures. The doses of benzodiazepines and phenobarbital required to terminate theophylline-induced seizures are close to the doses that may cause severe respiratory depression or respiratory arrest; the healthcare professional should therefore be prepared to provide assisted ventilation. Elderly patients and patients with COPD may be more susceptible to the respiratory depressant effects of anticonvulsants. Barbiturate-induced coma or administration of general anesthesia may be required to terminate repetitive seizures or status epilepticus. General anesthesia should be used with caution in patients with theophylline overdose because fluorinated volatile anesthetics may sensitize the myocardium to endogenous catecholamines released by theophylline. Enflurane appears less likely to be associated with this effect than halothane and may, therefore, be safer. Neuromuscular blocking agents alone should not be used to terminate seizures since they abolish the musculoskeletal manifestations without terminating seizure activity in the brain.
4. Anticipate Need for Anticonvulsants In patients with theophylline overdose who are at high risk for theophylline-induced seizures, e.g., patients with acute overdoses and serum theophylline concentrations >100 mcg/mL or chronic overdosage in patients >60 years of age with serum theophylline concentrations >30 mcg/mL, the need for anticonvulsant therapy should be anticipated. A benzodiazepine such as diazepam should be drawn into a syringe and kept at the patient’s bedside and medical personnel qualified to treat seizures should be immediately available. In selected patients at high risk for theophylline-induced seizures, consideration should be given to the administration of prophylactic anticonvulsant therapy. Situations where prophylactic anticonvulsant therapy should be considered in high risk patients include anticipated delays in instituting methods for extracorporeal removal of theophylline (e.g., transfer of a high risk patient from one healthcare facility to another for extracorporeal removal) and clinical circumstances that significantly interfere with efforts to enhance theophylline clearance (e.g., a neonate where dialysis may not be technically feasible or a patient with vomiting unresponsive to antiemetics who is unable to tolerate multiple-dose oral activated charcoal). In animal studies, prophylactic administration of phenobarbital, but not phenytoin, has been shown to delay the onset of theophylline-induced generalized seizures and to increase the dose of theophylline required to induce seizures (i.e., markedly increases the LD50). Although there are no controlled studies in humans, a loading dose of intravenous phenobarbital (20 mg/kg infused over 60 minutes) may delay or prevent life-threatening seizures in high risk patients while efforts to enhance theophylline clearance are continued. Phenobarbital may cause respiratory depression, particularly in elderly patients and patients with COPD.
5. Treatment of cardiac arrhythmias Sinus tachycardia and simple ventricular premature beats are not harbingers of life-threatening arrhythmias, they do not require treatment in the absence of hemodynamic compromise, and they resolve with declining serum theophylline concentrations. Other arrhythmias, especially those associated with hemodynamic compromise, should be treated with antiarrhythmic therapy appropriate for the type of arrhythmia.
6. Gastrointestinal decontamination Oral activated charcoal (0.5 g/kg up to 20 g and repeat at least once 1 to 2 hours after the first dose) is extremely effective in blocking the absorption of theophylline throughout the gastrointestinal tract, even when administered several hours after ingestion. If the patient is vomiting, the charcoal should be administered through a nasogastric tube or after administration of an antiemetic. Phenothiazine antiemetics such as prochlorperazine or perphenazine should be avoided since they can lower the seizure threshold and frequently cause dystonic reactions. A single dose of sorbitol may be used to promote stooling to facilitate removal of theophylline bound to charcoal from the gastrointestinal tract. Sorbitol, however, should be dosed with caution since it is a potent purgative which can cause profound fluid and electrolyte abnormalities, particularly after multiple doses. Commercially available fixed combinations of liquid charcoal and sorbitol should be avoided in young children and after the first dose in adolescents and adults since they do not allow for individualization of charcoal and sorbitol dosing. Ipecac syrup should be avoided in theophylline overdoses. Although ipecac induces emesis, it does not reduce the absorption of theophylline unless administered within 5 minutes of ingestion and even then is less effective than oral activated charcoal. Moreover, ipecac induced emesis may persist for several hours after a single dose and significantly decrease the retention and the effectiveness of oral activated charcoal.
7. Serum Theophylline Concentration Monitoring The serum theophylline concentration should be measured immediately upon presentation, 2 to 4 hours later, and then at sufficient intervals, e.g., every 4 hours, to guide treatment decisions and to assess the effectiveness of therapy. Serum theophylline concentrations may continue to increase after presentation of the patient for medical care as a result of continued absorption of theophylline from the gastrointestinal tract. Serial monitoring of serum theophylline serum concentrations should be continued until it is clear that the concentration is no longer rising and has returned to non-toxic levels.
8. General Monitoring Procedures Electrocardiographic monitoring should be initiated on presentation and continued until the serum theophylline level has returned to a non-toxic level. Serum electrolytes and glucose should be measured on presentation and at appropriate intervals indicated by clinical circumstances. Fluid and electrolyte abnormalities should be promptly corrected. Monitoring and treatment should be continued until the serum concentration decreases below 20 mcg/mL.
9. Enhance clearance of theophylline Multiple-dose oral activated charcoal (e.g., 0.5 mg/kg up to 20 g, every two hours) increases the clearance of theophylline at least twofold by adsorption of theophylline secreted into gastrointestinal fluids. Charcoal must be retained in, and pass through, the gastrointestinal tract to be effective; emesis should therefore be controlled by administration of appropriate antiemetics. Alternatively, the charcoal can be administered continuously through a nasogastric tube in conjunction with appropriate antiemetics. A single dose of sorbitol may be administered with the activated charcoal to promote stooling to facilitate clearance of the adsorbed theophylline from the gastrointestinal tract. Sorbitol alone does not enhance clearance of theophylline and should be dosed with caution to prevent excessive stooling which can result in severe fluid and electrolyte imbalances. Commercially available fixed combinations of liquid charcoal and sorbitol should be avoided in young children and after the first dose in adolescents and adults since they do not allow for individualization of charcoal and sorbitol dosing. In patients with intractable vomiting, extracorporeal methods of theophylline removal should be instituted (see OVERDOSAGE, Extracorporeal Removal).

Specific Recommendations

Acute Overdose

A. Serum Concentration >20<30 mcg/mL

- Administer a single dose of oral activated charcoal.
- Monitor the patient and obtain a serum theophylline concentration in 2 to 4 hours to insure that the concentration is not increasing.

B. Serum Concentration >30 <100 mcg/mL

- Administer multiple dose oral activated charcoal and measures to control emesis.
- Monitor the patient and obtain serial theophylline concentrations every 2 to 4 hours to gauge the effectiveness of therapy and to guide further treatment decisions.
- Institute extracorporeal removal if emesis, seizures, or cardiac arrhythmias cannot be adequately controlled (see OVERDOSAGE, Extracorporeal Removal).

C. Serum Concentration >100 mcg/mL

- Consider prophylactic anticonvulsant therapy.
- Administer multiple-dose oral activated charcoal and measures to control emesis.
- Consider extracorporeal removal, even if the patient has not experienced a seizure (see OVERDOSAGE, Extracorporeal Removal).
- Monitor the patient and obtain serial theophylline concentrations every 2 to 4 hours to gauge the effectiveness of therapy and to guide further treatment decisions.

Chronic Overdosage

A. Serum Concentration >20 <30 mcg/mL (with manifestations of theophylline toxicity)

- Administer a single dose of oral activated charcoal.
- Monitor the patient and obtain a serum theophylline concentration in 2 to 4 hours to insure that the concentration is not increasing.

B. Serum Concentration >30 mcg/mL in patients <60 years of age

- Administer multiple-dose oral activated charcoal and measures to control emesis.
- Monitor the patient and obtain serial theophylline concentrations every 2 to 4 hours to gauge the effectiveness of therapy and to guide further treatment decisions.
- Institute extracorporeal removal if emesis, seizures, or cardiac arrhythmias cannot be adequately controlled (see OVERDOSAGE, Extracorporeal Removal).

C. Serum Concentration >30 mcg/mL in patients ≥ 60 years of age

- Consider prophylactic anticonvulsant therapy.
- Administer multiple-dose oral activated charcoal and measures to control emesis.
- Consider extracorporeal removal even if the patient has not experienced a seizure (see OVERDOSAGE, Extracorporeal Removal).
- Monitor the patient and obtain serial theophylline concentrations every 2 to 4 hours to gauge the effectiveness of therapy and to guide further treatment decisions.

Extracorporeal Removal

Increasing the rate of theophylline clearance by extracorporeal methods may rapidly decrease serum concentrations, but the risks of the procedure must be weighed against the potential benefit. Charcoal hemoperfusion is the most effective method of extracorporeal removal, increasing theophylline clearance up to sixfold, but serious complications, including hypotension, hypocalcemia, platelet consumption and bleeding diatheses may occur. Hemodialysis is about as efficient as multiple-dose oral activated charcoal and has a lower risk of serious complications than charcoal hemoperfusion. Hemodialysis should be considered as an alternative when charcoal hemoperfusion is not feasible and multiple-dose oral charcoal is ineffective because of intractable emesis. Serum theophylline concentrations may rebound 5-10 mcg/mL after discontinuation of charcoal hemoperfusion or hemodialysis due to redistribution of theophylline from the tissue compartment. Peritoneal dialysis is ineffective for theophylline removal; exchange transfusions in neonates have been minimally effective.

DOSAGE AND ADMINISTRATION

Theophylline 400 or 600 mg extended-release tablets can be taken once a day in the morning or evening. It is recommended that theophylline extended-release tablets be taken with meals. Patients should be advised that if they choose to take theophylline extended-release tablets with food it should be taken consistently with food and if they take it in a fasted condition it should routinely be taken fasted. It is important that the product whenever dosed be dosed consistently with or without food.

Theophylline extended-release tablets are not to be chewed or crushed because it may lead to a rapid release of theophylline with the potential for toxicity. The tablet may be split. Infrequently, patients receiving theophylline extended-release tablets 400 or 600 mg may pass an intact matrix tablet in the stool or via colostomy. These matrix tablets usually contain little or no residual theophylline.

Stabilized patients, 12 years of age or older, who are taking an immediate-release or controlled-release theophylline product may be transferred to once-daily administration of 400 mg or 600 mg theophylline extended-release tablets on a mg-for-mg basis.

It must be recognized that the peak and trough serum theophylline levels produced by the once-daily dosing may vary from those produced by the previous product and/or regimen.

General Considerations

The steady-state peak serum theophylline concentration is a function of the dose, the dosing interval, and the rate of theophylline absorption and clearance in the individual patient. Because of marked individual differences in the rate of theophylline clearance, the dose required to achieve a peak serum theophylline concentration in the 10 to 20 mcg/mL range varies fourfold among otherwise similar patients in the absence of factors known to alter theophylline clearance (e.g., 400 to 1600 mg/day in adults <60 years old and 10 to 36 mg/kg/day in children 1 to 9 years old). For a given population there is no single theophylline dose that will provide both safe and effective serum concentrations for all patients. Administration of the median theophylline dose required to achieve a therapeutic serum theophylline concentration in a given population may result in either sub-therapeutic or potentially toxic serum theophylline concentrations in individual patients. For example, at a dose of 900 mg/d in adults <60 years or 22 mg/kg/d in children 1 to years, the steady-state peak serum theophylline concentration will be <10 mcg/mL in about 30% of patients, 10 to 20 mcg/mL in about 50% and 20 to 30 mcg/mL in about 20% of patients. The dose of theophylline must be individualized on the basis of peak serum theophylline concentration measurements in order to achieve a dose that will provide maximum potential benefit with minimal risk of adverse effects.

Transient caffeine-like adverse effects and excessive serum concentrations in slow metabolizers can be avoided in most patients by starting with a sufficiently low dose and slowly increasing the dose, if judged to be clinically indicated, in small increments (See Table V). Dose increases should only be made if the previous dosage is well tolerated and at intervals of no less than 3 days to allow serum theophylline concentrations to reach the new steady-state. Dosage adjustment should be guided by serum theophylline concentration measurement (see PRECAUTIONS, Laboratory Tests and DOSAGE AND ADMINISTRATION, Table VI). Healthcare providers should instruct patients and caregivers to discontinue any dosage that causes adverse effects, to withhold the medication until these symptoms are gone and to then resume therapy at a lower, previously tolerated dosage (see WARNINGS).

If the patient’s symptoms are well controlled, there are no apparent adverse effects, and no intervening factors that might alter dosage requirements (see WARNINGS and PRECAUTIONS), serum theophylline concentrations should be monitored at 6 month intervals for rapidly growing children and at yearly intervals for all others. In acutely ill patients, serum theophylline concentrations should be monitored at frequent intervals, e.g., every 24 hours.

Theophylline distributes poorly into body fat, therefore, mg/kg dose should be calculated on the basis of ideal body weight.

Table V contains theophylline dosing titration schema recommended for patients in various age groups and clinical circumstances. Table VI contains recommendations for theophylline dosage adjustment based upon serum theophylline concentrations. Application of these general dosing recommendations to individual patients must take into account the unique clinical characteristics of each patient. In general, these recommendations should serve as the upper limit for dosage adjustments in order to decrease the risk of potentially serious adverse events associated with unexpected large increases in serum theophylline concentration.

A. Children (12 to 15 years) and adults (16 to 60 years) without risk factors for impaired clearance.

Table V. Dosing initiation and titration (as anhydrous theophylline). [Patients with more rapid metabolism clinically identified by higher than average dose requirements, should receive a smaller dose more frequently (every 12 hours) to prevent breakthrough symptoms resulting from low trough concentrations before the next dose.]
 | Titration Step | Children < 45 kg | Children > 45 kg and adults
1. | Starting Dosage | 12 to 14 mg/kg/day up to a maximum of 300 mg/day admin. QD | 300 to 400 mg/day [If caffeine-like adverse effects occur, then consideration should be given to a lower dose and titrating the dose more slowly (see ADVERSE REACTIONS).] admin. QD
2. | After 3 days, if tolerated, increase dose to: | 16 mg/kg/day up to a maximum of 400 mg/day admin. QD | 400 to 600 mg/day admin. QD
3. | After 3 more days, if tolerated, and if needed increase dose to: | 20 mg/kg/day up to a maximum of 600 mg/day admin. QD | As with all theophylline products, doses greater than 600 mg should be titrated according to blood level (see Table VI)

B. Patients With Risk Factors For Impaired Clearance, The Elderly (>60 Years), And Those In Whom It Is Not Feasible To Monitor Serum Theophylline Concentrations:

In children 12 to 15 years of age, the theophylline dose should not exceed 16 mg/kg/day up to a maximum of 400 mg/day in the presence of risk factors for reduced theophylline clearance (see WARNINGS) or if it is not feasible to monitor serum theophylline concentrations.

In adolescents ≥16 years and adults, including the elderly, the theophylline dose should not exceed 400 mg/day in the presence of risk factors for reduced theophylline clearance (see WARNINGS) or if it is not feasible to monitor serum theophylline concentrations.

Table VI. Dosage adjustment guided by serum theophylline concentration.
Peak Serum Concentration | Dosage Adjustment
< 9.9 mcg/mL | If symptoms are not controlled and current dosage is tolerated, increase dose about 25%. Recheck serum concentration after three days for further dosage adjustment.
10-14.9 mcg/mL | If symptoms are controlled and current dosage is tolerated, maintain dose and recheck serum concentration at 6 to 12 month intervals. [Dose reduction and/or serum theophylline concentration measurement is indicated whenever adverse effects are present physiologic abnormalities that can reduce theophylline clearance occur (e.g. sustained fever), or a drug that interacts with theophylline is added or discontinued (see WARNINGS).] If symptoms are not controlled and current dosage is tolerated consider adding additional medication(s) to treatment regimen.
15-19.9 mcg/mL | Consider 10% decrease in dose to provide greater margin of safety even if current dosage is tolerated.
20-24.9 mcg/mL | Decrease dose by 25% even if no adverse effects are present. Recheck serum concentration after 3 days to guide further dosage adjustment.
25-30 mcg/mL | Skip next dose and decrease subsequent doses at least 25% even if no adverse effects are present. Recheck serum concentration after 3 days to guide further dosage adjustment. If symptomatic, consider whether overdose treatment is indicated (see recommendations for chronic overdosage).
> 30 mcg/mL | Treat overdose as indicated (see recommendations for chronic overdosage). If theophylline is subsequently resumed, decrease dose by at least 50% and recheck serum concentration after 3 days to guide further dosage adjustment.

HOW SUPPLIED

Theophylline (Anhydrous) Extended-Release Tablets 400 mg are supplied in

CRC bottles containing 100 tablets (NDC 68462-380-01) and non-CRC bottles containing 500 tablets (NDC 68462-380-05).

Each white to off-white, round shaped, uncoated 400 mg tablet is debossed with ‘G70’ on either side of the break line and ‘400’ on the other side.

Theophylline (Anhydrous) Extended-Release Tablets 600 mg are supplied in CRC bottles containing 100 tablets (NDC 68462-356-01) and non-CRC bottles containing 500 tablets (NDC 68462-356-05).

Each white to off-white rectangular shaped, uncoated 600 mg tablet is debossed with ‘G70’ on either side of the score line and ‘600’ on the other side.

STORAGE AND HANDLING

Store at 25°C (77°F); excursions permitted between 15°C to 30°C (59°F to 86°F).

Dispense in a tight, light-resistant container.

Distributed by:

Glenmark Pharmaceuticals Inc., USA
Elmwood Park, NJ 07407

Questions? 1 (888) 721-7115
www.glenmarkpharma-us.com
August 2025

Principal Display Panel - 400 mg

NDC 68462-380-01

Theophylline (Anhydrous) Extended-Release Tablets

400 mg

100 Tablets

Principal Display Panel - 600 mg

NDC 68462-356-01

Theophylline (Anhydrous) Extended-Release Tablets

600 mg

100 Tablets